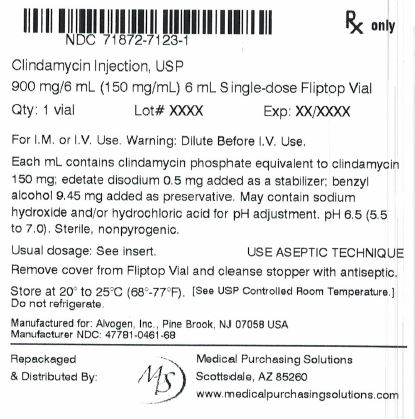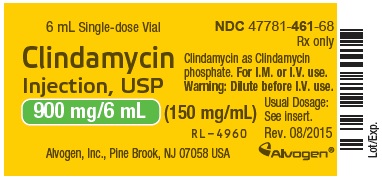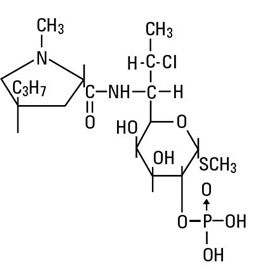 DRUG LABEL: Clindamycin
NDC: 71872-7123 | Form: INJECTION, SOLUTION, CONCENTRATE
Manufacturer: Medical Purchasing Solutions, LLC
Category: prescription | Type: HUMAN PRESCRIPTION DRUG LABEL
Date: 20200124

ACTIVE INGREDIENTS: CLINDAMYCIN PHOSPHATE 150 mg/1 mL
INACTIVE INGREDIENTS: EDETATE DISODIUM 0.5 mg/1 mL; BENZYL ALCOHOL 9.45 mg/1 mL; SODIUM HYDROXIDE; HYDROCHLORIC ACID

To reduce the development of drug-resistant bacteria and maintain the effectiveness of clindamycin and other antibacterial drugs, clindamycin should be used only to treat or prevent infections that are proven or strongly suspected to be caused by bacteria. Clindamycin Injection USP is for Intramuscular and Intravenous Use.

WARNING

Clostridium difficile-associated diarrhea (CDAD) has been reported with use of nearly all antibacterial agents, including clindamycin, and may range in severity from mild diarrhea to fatal colitis. Treatment with antibacterial agents alters the normal flora of the colon leading to overgrowth of C. difficile.

Because clindamycin therapy has been associated with severe colitis which may end fatally, it should be reserved for serious infections where less toxic antimicrobial agents are inappropriate, as described in the INDICATIONS AND USAGE section. It should not be used in patients with nonbacterial infections such as most upper respiratory tract infections. C. difficile produces toxins A and B which contribute to the development of CDAD. Hypertoxin producing strains of C. difficile cause increased morbidity and mortality, as these infections can be refractory to antimicrobial therapy and may require colectomy. CDAD must be considered in all patients who present with diarrhea following antibiotic use. Careful medical history is necessary since CDAD has been reported to occur over two months after the administration of antibacterial agents.

If CDAD is suspected or confirmed, ongoing antibiotic use not directed against C. difficile may need to be discontinued. Appropriate fluid and electrolyte management, protein supplementation, antibiotic treatment of C. difficile, and surgical evaluation should be instituted as clinically indicated.

DESCRIPTION

Clindamycin Injection, USP, a water soluble ester of clindamycin and phosphoric acid, is a sterile solution for intramuscular or intravenous use.

May contain sodium hydroxide and/or hydrochloric acid for pH adjustment. pH is 6.5 range 5.5 to 7.0.

Clindamycin is a semisynthetic antibiotic produced by a 7(S)-chloro- substitution of the 7 (R)‑hydroxyl group of the parent compound lincomycin.

The chemical name of clindamycin phosphate is methyl 7-chloro-6,7,8-trideoxy-6-(1-methyl- trans-4-propyl-L-2-pyrrolidinecarboxamido)-1-thio-L- threo-α-D- galacto-octopyranoside 2‑(dihydrogen phosphate).

The molecular formula is C18H34ClN2O8PS and the molecular weight is 504.97.

The structural formula is represented below:

Each mL contains clindamycin phosphate equivalent to 150 mg clindamycin, 0.5 mg disodium edetate and 9.45 mg benzyl alcohol added as a preservative.

CLINICAL PHARMACOLOGY

Distribution

Biologically inactive clindamycin phosphate is converted to active clindamycin.

By the end of short-term intravenous infusion, peak serum levels of active clindamycin are reached.

After intramuscular injection of clindamycin phosphate, peak levels of active clindamycin are reached within 3 hours in adults and 1 hour in pediatric patients. Serum level curves may be constructed from IV peak serum levels as given in Table 1 by application of elimination half-lives (see Excretion).

Serum levels of clindamycin can be maintained above the in vitro minimum inhibitory concentrations for most indicated organisms by administration of clindamycin phosphate every 8 to 12 hours in adults and every 6 to 8 hours in pediatric patients, or by continuous intravenous infusion. An equilibrium state is reached by the third dose.

No significant levels of clindamycin are attained in the cerebrospinal fluid even in the presence of inflamed meninges.

Metabolism

In vitro studies in human liver and intestinal microsomes indicated that clindamycin is predominantly metabolized by Cytochrome P450 3A4 (CYP3A4), with minor contribution from CYP3A5, to form clindamycin sulfoxide and a minor metabolite, N-desmethylclindamycin.

Excretion

Biologically inactive clindamycin phosphate disappears rapidly from the serum; the average elimination half-life is 6 minutes; however, the serum elimination half-life of active clindamycin is about 3 hours in adults and 2½ hours in pediatric patients.

Special Populations

Renal/Hepatic Impairment

The elimination half-life of clindamycin is increased slightly in patients with markedly reduced renal or hepatic function. Hemodialysis and peritoneal dialysis are not effective in removing clindamycin from the serum. Dosage schedules need not be modified in the presence of mild or moderate renal or hepatic disease.

Use in Elderly

Pharmacokinetic studies in elderly volunteers (61 to 79 years) and younger adults (18 to 39 years) indicate that age alone does not alter clindamycin pharmacokinetics (clearance, elimination half-life, volume of distribution, and area under the serum concentration-time curve) after IV administration of clindamycin phosphate. After oral administration of clindamycin hydrochloride, elimination half-life is increased to approximately 4.0 hours (range 3.4 to 5.1 h) in the elderly, compared to 3.2 hours (range 2.1 to 4.2 h) in younger adults. The extent of absorption, however, is not different between age groups and no dosage alteration is necessary for the elderly with normal hepatic function and normal (age-adjusted) renal function^1.

Serum assays for active clindamycin require an inhibitor to prevent in vitro hydrolysis of clindamycin phosphate.

Table 1. Average Peak and Trough Serum Concentrations of Active Clindamycin After Dosing with Clindamycin Phosphate

Dosage Regimen | Peak mcg/mL | Trough mcg/mL
Healthy Adult Males (Post equilibrium)
600 mg IV in 30 min q6h | 10.9 | 2
600 mg IV in 30 min q8h | 10.8 | 1.1
900 mg IV in 30 min q8h | 14.1 | 1.7
600 mg IM q12h* | 9
Pediatric Patients (first dose)*
5-7 mg/kg IV in 1 hour | 10
5-7 mg/kg IM | 8
3-5 mg/kg IM | 4

*Data in this group from patients being treated for infection

Microbiology

Mechanism of Action
Clindamycin inhibits bacterial protein synthesis by binding to the 23S RNA of the 50S subunit of the ribosome. Clindamycin is bacteriostatic.

Resistance
Resistance to clindamycin is most often caused by modification of specific bases of the 23S ribosomal RNA. Cross-resistance between clindamycin and lincomycin is complete. Because the binding sites for these antibacterial drugs overlap, cross-resistance is sometimes observed among lincosamides, macrolides and streptogramin B. Macrolide-inducible resistance to clindamycin occurs in some isolates of macrolide-resistant bacteria. Macrolide-resistant isolates of staphylococci and beta-hemolytic streptococci should be screened for induction of clindamycin resistance using the D-zone test.

Antimicrobial Activity

Clindamycin has been shown to be active against most of the isolates of the following microorganisms, both in vitro and in clinical infections, as described in the INDICATIONS AND USAGEsection.

Gram-positive Bacteria

Staphylococcus aureus (methicillin-susceptible strains)
Streptococcus pneumoniae (penicillin-susceptible strains)
Streptococcus pyogenes

Anaerobic Bacteria

Clostridium perfringens
Fusobacterium necrophorum
Fusobacterium nucleatum
Peptostreptococcus anaerobius
Prevotella melaninogenica

At least 90% of the microorganisms listed below exhibit in vitro minimum inhibitory concentrations (MICs) less than or equal to the clindamycin susceptible MIC breakpoint for organisms of a similar type to those shown in Table 2. However, the efficacy of clindamycin in treating clinical infections due to these microorganisms has not been established in adequate and well-controlled clinical trials.

Gram-positive Bacteria

Staphylococcus epidermidis (methicillin-susceptible strains)
Streptococcus agalactiae
Streptococcus anginosus
Streptococcus mitis
Streptococcus oralis

Anaerobic Bacteria

Actinomyces israelii
Clostridium clostridioforme
Eggerthella lenta
Finegoldia (Peptostreptococcus) magna
Micromonas (Peptostreptococcus) micros
Prevotella bivia
Prevotella intermedia
Propionibacterium acnes

Susceptibility Testing Methods

When available, the clinical microbiology laboratory should provide cumulative in vitro susceptibility test results for antimicrobial drugs used in local hospitals and practice areas to the physician as periodic reports that describe the susceptibility profile of nosocomial and community-acquired pathogens. These reports should aid the physician in selecting an antibacterial drug for treatment.

Dilution Techniques

Quantitative methods are used to determine antimicrobial minimum inhibitory concentrations (MICs). These MICs provide estimates of the susceptibility of bacteria to antimicrobial compounds. The MICs should be determined using a standardized test method^2,3 (broth and/or agar). The MIC values should be interpreted according to the criteria provided in Table 2.

Diffusion Techniques

Quantitative methods that require the measurement of zone diameters can also provide reproducible estimates of the susceptibility of bacteria to antimicrobial compounds. The zone size should be determined using a standardized method^2,5. This procedure uses paper disks impregnated with 2 mcg of clindamycin to test the susceptibility of bacteria to clindamycin. The disk diffusion breakpoints are provided in Table 2.

Anaerobic Techniques
For anaerobic bacteria, the susceptibility to clindamycin can be determined by a standardized test method^2,4. The MIC values obtained should be interpreted according to the criteria provided in Table 2.

Table 2. Susceptibility Test Interpretive Criteria for Clindamycin

Pathogen | Susceptibility Interpretive Criteria
Pathogen | Minimal Inhibitory Concentrations (MIC in mcg/mL) |  |  | Disk Diffusion (Zone Diameters in mm)
Pathogen | S | I | R | S | I | R
Staphylococcus spp. | ≤0.5 | 1-2 | ≥4 | ≥21 | 15-20 | ≤14
Streptococcus pneumoniae and other Streptococcus spp. | ≤0.25 | 0.5 | ≥1 | ≥19 | 16-18 | ≤15
Anaerobic Bacteria | ≤2 | 4 | ≥8 | NA | NA | NA

NA=not applicable

A report of Susceptible (S) indicates that the antimicrobial drug is likely to inhibit growth of the pathogen if the antimicrobial drug reaches the concentration usually achievable at the site of infection. A report of Intermediate (I) indicates that the result should be considered equivocal, and, if the microorganism is not fully susceptible to alternative, clinically feasible drugs, the test should be repeated. This category implies possible clinical applicability in body sites where the drug is physiologically concentrated or in situations where high dosage of drug can be used. This category also provides a buffer zone that prevents small, uncontrolled technical factors from causing major discrepancies in interpretation. A report of Resistant (R) indicates that the antimicrobial drug is not likely to inhibit growth of the pathogen if the antimicrobial drug reaches the concentration usually achievable at the infection site; other therapy should be selected.

Quality Control

Standardized susceptibility test procedures require the use of laboratory controls to monitor and ensure the accuracy and precision of the supplies and reagents used in the assay, and the techniques of the individuals performing the test.^2,3,4,5 Standard clindamycin powder should provide the MIC ranges in Table 3. For the disk diffusion technique using the 2 mcg clindamycin disk the criteria provided in Table 2 should be achieved.

Table 3. Acceptable Quality Control Ranges for Clindamycin

QC Strain | Acceptable Quality Control Ranges
QC Strain | Minimum Inhibitory Concentration Range (mcg/mL) | Disk Diffusion Range (Zone Diameters in mm)
Enterococcus faecalis^1 ATCC 29212 | 4-16 | NA
Staphylococcus aureus ATCC 29213 | 0.06-0.25 | NA
Staphylococcus aureus ATCC 25923 | NA | 24-30
Streptococcus pneumoniae ATCC 49619 | 0.03-0.12 | 19-25
Bacteroides fragilis ATCC 25285 | 0.5-2 | NA
Bacteroides thetaiotaomicron ATCC 29741 | 2-8 | NA
Clostridium difficile^2 ATCC 700057 | 2-8 | NA
Eggerthella lenta ATCC 43055 | 0.06-0.25 | NA

1. Enterococcus faecalis has been included in this table for quality control purposes only.
2. Quality control for C. difficile is performed using the agar dilution method only, all other obligate anaerobes may be tested by either broth microdilution or agar dilution methods.
NA=Not applicable
ATCC® is a registered trademark of the American Type Culture Collection

INDICATIONS AND USAGE

Clindamycin Injection, USP is indicated in the treatment of serious infections caused by susceptible anaerobic bacteria.

Clindamycin Injection, USP is also indicated in the treatment of serious infections due to susceptible strains of streptococci, pneumococci, and staphylococci. Its use should be reserved for penicillin-allergic patients or other patients for whom, in the judgment of the physician, a penicillin is inappropriate. Because of the risk of antibiotic-associated pseudomembranous colitis, as described in the BOXED WARNING, before selecting clindamycin the physician should consider the nature of the infection and the suitability of less toxic alternatives (e.g., erythromycin).

Bacteriologic studies should be performed to determine the causative organisms and their susceptibility to clindamycin.

Indicated surgical procedures should be performed in conjunction with antibiotic therapy.

Clindamycin Injection, USP is indicated in the treatment of serious infections caused by susceptible strains of the designated organisms in the conditions listed below:

Lower respiratory tract infections including pneumonia, empyema, and lung abscess caused by anaerobes, Streptococcus pneumoniae, other streptococci (except E. faecalis), and Staphylococcus aureus.

Skin and skin structure infections caused by Streptococcus pyogenes, Staphylococcus aureus, and anaerobes.

Gynecological infections including endometritis, nongonococcal tubo-ovarian abscess, pelvic cellulitis, and postsurgical vaginal cuff infection caused by susceptible anaerobes.

Intra-abdominal infections including peritonitis and intra-abdominal abscess caused by susceptible anaerobic organisms.

Septicemia caused by Staphylococcus aureus, streptococci (except Enterococcus faecalis), and susceptible anaerobes.

Bone and joint infections including acute hematogenous osteomyelitis caused by Staphylococcus aureus and as adjunctive therapy in the surgical treatment of chronic bone and joint infections due to susceptible organisms.

To reduce the development of drug-resistant bacteria and maintain the effectiveness of clindamycin and other antibacterial drugs, clindamycin should be used only to treat or prevent infections that are proven or strongly suspected to be caused by susceptible bacteria. When culture and susceptibility information are available, they should be considered in selecting or modifying antibacterial therapy. In the absence of such data, local epidemiology and susceptibility patterns may contribute to the empiric selection of therapy.

CONTRAINDICATIONS

This drug is contraindicated in individuals with a history of hypersensitivity to preparations containing clindamycin or lincomycin.

WARNINGS

See BOXED WARNING.

Clostridium difficile Associated Diarrhea

Clostridium difficile associated diarrhea (CDAD) has been reported with use of nearly all antibacterial agents, including clindamycin, and may range in severity from mild diarrhea to fatal colitis. Treatment with antibacterial agents alters the normal flora of the colon leading to overgrowth of C. difficile.

C. difficile produces toxins A and B which contribute to the development of CDAD. Hypertoxin producing strains of C. difficile cause increased morbidity and mortality, as these infections can be refractory to antimicrobial therapy and may require colectomy. CDAD must be considered in all patients who present with diarrhea following antibiotic use. Careful medical history is necessary since CDAD has been reported to occur over two months after the administration of antibacterial agents.

If CDAD is suspected or confirmed, ongoing antibiotic use not directed against C. difficile may need to be discontinued. Appropriate fluid and electrolyte management, protein supplementation, antibiotic treatment of C. difficile, and surgical evaluation should be instituted as clinically indicated.

Anaphylactic and Severe Hypersensitivity Reactions

Anaphylactic shock and anaphylactic reactions have been reported (see ADVERSE REACTIONS).

Severe hypersensitivity reactions, including severe skin reactions such as toxic epidermal necrolysis (TEN), drug reaction with eosinophilia and systemic symptoms (DRESS), and Stevens-Johnson syndrome (SJS), some with fatal outcome, have been reported (see ADVERSE REACTIONS).

In case of such an anaphylactic or severe hypersensitivity reaction, discontinue treatment permanently and institute appropriate therapy.

A careful inquiry should be made concerning previous sensitivities to drugs and other allergens.

Benzyl Alcohol Toxicity in Pediatric Patients (“Gasping Syndrome”)

This product contains benzyl alcohol as a preservative. The preservative benzyl alcohol has been associated with serious adverse events, including the “gasping syndrome”, and death in pediatric patients. Although normal therapeutic doses of this product ordinarily deliver amounts of benzyl alcohol that are substantially lower than those reported in association with the “gasping syndrome”, the minimum amount of benzyl alcohol at which toxicity may occur is not known.

The risk of benzyl alcohol toxicity depends on the quantity administered and the liver and kidneys’ capacity to detoxify the chemical. Premature and low birth weight infants may be more likely to develop toxicity.

Usage in Meningitis

Since clindamycin does not diffuse adequately into the cerebrospinal fluid, the drug should not be used in the treatment of meningitis.

PRECAUTIONS

General

Review of experience to date suggests that a subgroup of older patients with associated severe illness may tolerate diarrhea less well. When clindamycin is indicated in these patients, they should be carefully monitored for change in bowel frequency.

Clindamycin phosphate should be prescribed with caution in individuals with a history of gastrointestinal disease, particularly colitis.

Clindamycin phosphate should be prescribed with caution in atopic individuals.

Certain infections may require incision and drainage or other indicated surgical procedures in addition to antibiotic therapy.

The use of clindamycin phosphate may result in overgrowth of nonsusceptible organisms—particularly yeasts. Should superinfections occur, appropriate measures should be taken as indicated by the clinical situation.

Clindamycin phosphate should not be injected intravenously undiluted as a bolus, but should be infused over at least 10 to 60 minutes as directed in the DOSAGE AND ADMINISTRATION section.

Clindamycin dosage modification may not be necessary in patients with renal disease. In patients with moderate to severe liver disease, prolongation of clindamycin half-life has been found. However, it was postulated from studies that when given every eight hours, accumulation should rarely occur. Therefore, dosage modification in patients with liver disease may not be necessary. However, periodic liver enzyme determinations should be made when treating patients with severe liver disease.

Prescribing clindamycin in the absence of a proven or strongly suspected bacterial infection or a prophylactic indication is unlikely to provide benefit to the patient and increases the risk of the development of drug-resistant bacteria.

Information for Patients

Patients should be counseled that antibacterial drugs including clindamycin should only be used to treat bacterial infections. They do not treat viral infections (e.g., the common cold). When clindamycin is prescribed to treat a bacterial infection, patients should be told that although it is common to feel better early in the course of therapy, the medication should be taken exactly as directed. Skipping doses or not completing the full course of therapy may (1) decrease the effectiveness of the immediate treatment and (2) increase the likelihood that bacteria will develop resistance and will not be treatable by clindamycin or other antibacterial drugs in the future.

Diarrhea is a common problem caused by antibiotics which usually ends when the antibiotic is discontinued. Sometimes after starting treatment with antibiotics, patients can develop watery and bloody stools (with or without stomach cramps and fever) even as late as two or more months after having taken the last dose of the antibiotic. If this occurs, patients should contact their physician as soon as possible.

Laboratory Tests

During prolonged therapy periodic liver and kidney function tests and blood counts should be performed.

Drug Interactions

Clindamycin has been shown to have neuromuscular blocking properties that may enhance the action of other neuromuscular blocking agents. Therefore, it should be used with caution in patients receiving such agents.

Clindamycin is metabolized predominantly by CYP3A4, and to a lesser extent by CYP3A5, to the major metabolite clindamycin sulfoxide and minor metabolite N-desmethylclindamycin. Therefore inhibitors of CYP3A4 and CYP3A5 may increase plasma concentrations of clindamycin and inducers of these isoenzymes may reduce plasma concentrations of clindamycin. In the presence of strong CYP3A4 inhibitors, monitor for adverse reactions. In the presence of strong CYP3A4 inducers such as rifampicin, monitor for loss of effectiveness.

In vitro studies indicate that clindamycin does not inhibit CYP1A2, CYP2C9, CYP2C19, CYP2E1 or CYP2D6 and only moderately inhibits CYP3A4.

Antagonism has been demonstrated between clindamycin and erythromycin in vitro. Because of possible clinical significance, the two drugs should not be administered concurrently.

Carcinogenesis, Mutagenesis, Impairment of Fertility

Long term studies in animals have not been performed with clindamycin to evaluate carcinogenic potential. Genotoxicity tests performed included a rat micronucleus test and an Ames Salmonella reversion test. Both tests were negative.

Fertility studies in rats treated orally with up to 300 mg/kg/day (approximately 1.1 times the highest recommended adult human dose based on mg/m^2) revealed no effects on fertility or mating ability.

Pregnancy: Teratogenic Effects

In clinical trials with pregnant women, the systemic administration of clindamycin during the second and third trimesters, has not been associated with an increased frequency of congenital abnormalities.

Clindamycin should be used during the first trimester of pregnancy only if clearly needed. There are no adequate and well-controlled studies in pregnant women during the first trimester of pregnancy. Because animal reproduction studies are not always predictive of the human response, this drug should be used during pregnancy only if clearly needed.

Reproduction studies performed in rats and mice using oral doses of clindamycin up to 600 mg/kg/day (2.1 and 1.1 times the highest recommended adult human dose based on mg/m^2, respectively) or subcutaneous doses of clindamycin up to 250 mg/kg/day (0.9 and 0.5 times the highest recommended adult human dose based on mg/m^2, respectively) revealed no evidence of teratogenicity.

Clindamycin Injection USP contains benzyl alcohol. Benzyl alcohol can cross the placenta. See WARNINGS.

Nursing Mothers

Clindamycin has been reported to appear in breast milk in the range of 0.7 to 3.8 mcg/mL at dosages of 150 mg orally to 600 mg intravenously. Clindamycin has the potential to cause adverse effects on the breastfed infant’s gastrointestinal flora. If oral or intravenous clindamycin is required by a nursing mother, it is not a reason to discontinue breastfeeding, but an alternate drug may be preferred. Monitor the infant for possible adverse effects on the gastrointestinal flora, such as diarrhea, candidiasis (thrush, diaper rash) or rarely, blood in the stool indicating possible antibiotic-associated colitis.

The developmental and health benefits of breastfeeding should be considered along with the mother’s clinical need for clindamycin and any potential adverse effects on the breastfed child from clindamycin or from the underlying maternal condition.

Pediatric Use

When clindamycin phosphate injection is administered to the pediatric population (birth to 16 years) appropriate monitoring of organ system functions is desirable.

Usage in Newborns and Infants

This product contains benzyl alcohol as a preservative. Benzyl alcohol has been associated with a fatal “Gasping Syndrome” in premature infants. See WARNINGS.

The potential for the toxic effect in the pediatric population from chemicals that may leach from the single dose premixed IV preparation in plastic has not been evaluated. See WARNINGS.

Geriatric Use

Clinical studies of clindamycin did not include sufficient numbers of patients age 65 and over to determine whether they respond differently from younger patients. However, other reported clinical experience indicates that antibiotic-associated colitis and diarrhea (due to Clostridium difficile) seen in association with most antibiotics occur more frequently in the elderly (>60 years) and may be more severe. These patients should be carefully monitored for the development of diarrhea.

Pharmacokinetic studies with clindamycin have shown no clinically important differences between young and elderly subjects with normal hepatic function and normal (age-adjusted) renal function after oral or intravenous administration.

ADVERSE REACTIONS

The following reactions have been reported with the use of clindamycin.

Infections and Infestations

Clostridium difficile colitis

Gastrointestinal

Antibiotic-associated colitis (see WARNINGS), pseudomembranous colitis, abdominal pain, nausea and vomiting. The onset of pseudomembranous colitis symptoms may occur during or after antibacterial treatment (see WARNINGS). An unpleasant or metallic taste has been reported after intravenous administration of the higher doses of clindamycin phosphate.

Hypersensitivity Reactions

Maculopapular rash and urticaria have been observed during drug therapy. Generalized mild to moderate morbilliform-like skin rashes are the most frequently reported of all adverse reactions.

Severe skin reactions such as Toxic Epidermal Necrolysis, some with fatal outcome, have been reported (see WARNINGS). Cases of Acute Generalized Exanthematous Pustulosis (AGEP), erythema multiforme, some resembling Stevens-Johnson syndrome, have been associated with clindamycin. Anaphylactic shock, anaphylactic reaction and hypersensitivity have also been reported (see WARNINGS).

Skin and Mucous Membranes

Pruritus, vaginitis, angioedema and rare instances of exfoliative dermatitis have been reported (see Hypersensitivity Reactions).

Liver

Jaundice and abnormalities in liver function tests have been observed during clindamycin therapy.

Renal

Although no direct relationship of clindamycin to renal damage has been established, renal dysfunction as evidenced by azotemia, oliguria, and/or proteinuria has been observed.

Hematopoietic

Transient neutropenia (leukopenia) and eosinophilia have been reported. Reports of agranulocytosis and thrombocytopenia have been made. No direct etiologic relationship to concurrent clindamycin therapy could be made in any of the foregoing.

Immune System

Drug reaction with eosinophilia and systemic symptoms (DRESS) cases have been reported.

Local Reactions

Injection site irritation, pain, induration and sterile abscess have been reported after intramuscular injection and thrombophlebitis after intravenous infusion. Reactions can be minimized or avoided by giving deep intramuscular injections and avoiding prolonged use of indwelling intravenous catheters.

Musculoskeletal

Polyarthritis cases have been reported

Cardiovascular

Cardiopulmonary arrest and hypotension have been reported following too rapid intravenous administration (see DOSAGE AND ADMINISTRATION).

OVERDOSAGE

Significant mortality was observed in mice at an intravenous dose of 855 mg/kg and in rats at an oral or subcutaneous dose of approximately 2,618 mg/kg. In the mice, convulsions and depression were observed.

Hemodialysis and peritoneal dialysis are not effective in removing clindamycin from the serum.

DOSAGE AND ADMINISTRATION

If diarrhea occurs during therapy, this antibiotic should be discontinued. (See BOXED WARNING).

Clindamycin phosphate IM administration should be used undiluted.

Clindamycin phosphate IV administration should be diluted (see Dilution for IV use and IV infusion rates below).

Adults

Parenteral (IM or IV Administration):

Serious infections due to aerobic gram-positive cocci and the more susceptible anaerobes (NOT generally including Bacteroides fragilis, Peptococcus species and Clostridium species other than Clostridium perfringens):

600 to 1,200 mg/day in 2, 3 or 4 equal doses

More severe infections, particularly those due to proven or suspected Bacteroides fragilis, Peptococcus species, or Clostridium species other than Clostridium perfringens:

1,200 to 2,700 mg/day in 2, 3 or 4 equal doses

For more serious infections, these doses may have to be increased. In life threatening situations due to either aerobes or anaerobes these doses may be increased. Doses of as much as 4,800 mg daily have been given intravenously to adults. See Dilution for IV use and IV Infusion Rates section below.

Single intramuscular injections of greater than 600 mg are not recommended.

Alternatively, drug may be administered in the form of a single rapid infusion of the first dose followed by continuous IV infusion as follows:

To maintain serum clindamycin levels | Rapid infusion rate | Maintenance infusion rate
Above 4 mcg/mL | 10 mg/min for 30 min | 0.75 mg/min
Above 5 mcg/mL | 15 mg/min for 30 min | 1.00 mg/min
Above 6 mcg/mL | 20 mg/min for 30 min | 1.25 mg/min

Neonates (less than 1 month)

15 to 20 mg/kg/day in three to four equal doses. The lower dosage may be adequate for small prematures.

Pediatric patients (1 month of age to 16 years)

Parenteral (IM or IV) Administration: 20 to 40 mg/kg/day in 3 or 4 equal doses. The higher doses would be used for more severe infections. As an alternative to dosing on a body weight basis, pediatric patients may be dosed on the basis of square meters body surface: 350 mg/m^2/day for serious infections and 450 mg/m^2/day for more severe infections.

Parenteral therapy may be changed to clindamycin palmitate hydrochloride for oral solution or clindamycin hydrochloride capsules when the condition warrants and at the discretion of the physician.

In cases of β-hemolytic streptococcal infections, treatment should be continued for at least 10 days.

Dilution for IV use and IV Infusion Rates

The concentration of clindamycin in diluent for infusion should notexceed 18 mg per mL. Infusion rates should not exceed 30 mg per minute.

The usual infusion dilutions and rates are as follows:

Dose | Diluent | Time
300 mg | 50 mL | 10 min
600 mg | 50 mL | 20 min
900 mg | 50-100 mL | 30 min
1,200 mg | 100 mL | 40 min

Administration of more than 1,200 mg in a single 1-hour infusion is not recommended.

Parenteral drug products should be inspected visually for particulate matter and discoloration prior to administration, whenever solution and container permit.

Dilution and Compatibility

Physical and biological compatibility studies monitored for 24 hours at room temperature have demonstrated no inactivation or incompatibility with the use of clindamycin phosphate in IV solutions containing sodium chloride, glucose, calcium or potassium, and solutions containing vitamin B complex in concentrations usually used clinically. No incompatibility has been demonstrated with the antibiotics cephalothin, kanamycin, gentamicin, penicillin or carbenicillin.

The following drugs are physically incompatible with clindamycin phosphate: ampicillin sodium, phenytoin sodium, barbiturates, aminophylline, calcium gluconate, and magnesium sulfate.

The compatibility and duration of stability of drug admixtures will vary depending on concentration and other conditions.

Physico-Chemical Stability of Diluted Solutions of Clindamycin

Room Temperature: 6 mg/mL, 9 mg/mL, and 12 mg/mL (equivalent to clindamycin base) in 5% Dextrose Injection, 0.9% Sodium Chloride Injection, or Lactated Ringers Injection in glass bottles or minibags, demonstrated physical and chemical stability for at least 16 days at 25°C. Also, 18 mg/mL (equivalent to clindamycin base) in 5% Dextrose Injection, in minibags, demonstrated physical and chemical stability for at least 16 days at 25°C.

Refrigeration: 6 mg/mL, 9 mg/mL, and 12 mg/mL (equivalent to clindamycin base) in 5% Dextrose Injection, 0.9% Sodium Chloride Injection, or Lactated Ringers Injection in glass bottles or minibags, demonstrated physical and chemical stability for at least 32 days at 4°C.

IMPORTANT: This chemical stability information in no way indicates that it would be acceptable practice to use this product well after the preparation time. Good professional practice suggests that compounded admixtures should be administered as soon after preparation as is feasible.

Frozen: 6 mg/mL, 9 mg/mL and 12 mg/mL (equivalent to clindamycin base) in 5% Dextrose Injection, 0.9% Sodium Chloride Injection, or Lactated Ringers Injection in minibags demonstrated physical and chemical stability for at least eight weeks at -10°C.

Frozen solutions should be thawed at room temperature and not refrozen.

HOW SUPPLIED

Each mL of Clindamycin Injection USP (150 mg/mL) contains clindamycin phosphate equivalent to 150 mg clindamycin, 0.5 mg disodium edetate, and 9.45 mg benzyl alcohol added as preservative. When necessary, pH is adjusted with sodium hydroxide and/or hydrochloric acid.

Clindamycin Injection, USP (150 mg/mL) is supplied as follows:

NDC No. | Volume | Type Container | Clindamycin base Total Content
47781-459-68 | 2 mL | Single-dose fliptop vial/25 vials per tray | 300 mg
47781-460-68 | 4 mL | Single-dose fliptop vial/25 vials per tray | 600 mg
47781-461-68 | 6 mL | Single-dose fliptop vial/25 vials per tray | 900 mg

Store at 20 to 25°C (68 to 77°F) [see USP Controlled Room Temperature.]
Do not refrigerate.

REFERENCES

1. Smith RB, Phillips JP: Evaluation of CLEOCIN HCl and CLEOCIN Phosphate in an Aged Population. Upjohn TR 8147-82-9122-021, December 1982.

2. CLSI. Performance Standards for Antimicrobial Susceptibility Testing: 26th ed. CLSI supplement M100S. Wayne, PA: Clinical and Laboratory Standards Institute; 2016.

3. CLSI. Methods for Dilution Antimicrobial Susceptibility Tests for Bacteria that Grow Aerobically; Approved Standard - Tenth Edition. CLSI document M07-A10. Wayne, PA: Clinical and Laboratory Standards Institute; 2015.

4. CLSI. Methods for Antimicrobial Susceptibility Testing of Anaerobic Bacteria; Approved Standard-Eighth Edition. CLSI document M11-A8. Wayne, PA: Clinical and Laboratory Standards Institute; 2012.

5. CLSI. Performance Standards for Antimicrobial Disk Susceptibility Tests; Approved Standard - Twelfth Edition. CLSI document M02-A12. Wayne, PA: Clinical and Laboratory Standards Institute; 2015.

Distributed by:
Alvogen, Inc.
Pine Brook, NJ 07058 USA

Pl459-03
Rev: 06/2017

OUTER PACKAGE LABEL

NDC 71872-7123-1

Clindamycin Injection, USP Rx only

900 mg/6 mL (150 mg/mL)

6mL Single-dose Fliptop Vial

For I.M. or I.V. Use. Warning: Dilute Before I.V. Use.

VIAL LABEL

6 mL Single-dose Vial
Rx only

Clindamycin
Injection, USP

900 mg/6mL (150 mg/mL)

Alvogen, Inc., Pine Brook, NJ 07058 USA Alvogen®